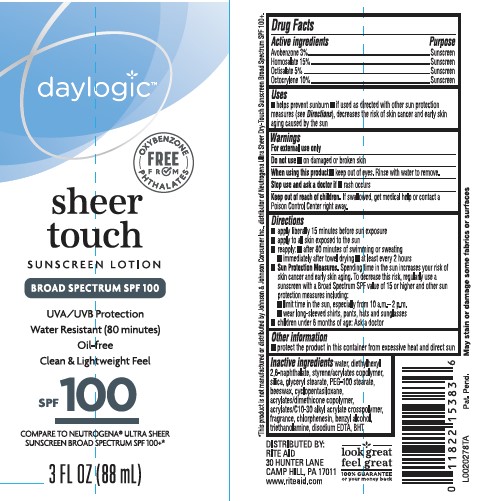 DRUG LABEL: SUNSCREEN
NDC: 11822-0922 | Form: LOTION
Manufacturer: Rite Aid Corporation
Category: otc | Type: HUMAN OTC DRUG LABEL
Date: 20260130

ACTIVE INGREDIENTS: AVOBENZONE 30 mg/1 mL; HOMOSALATE 150 mg/1 mL; OCTISALATE 50 mg/1 mL; OCTOCRYLENE 100 mg/1 mL
INACTIVE INGREDIENTS: WATER; DIETHYLHEXYL 2,6-NAPHTHALATE; STYRENE/ACRYLAMIDE COPOLYMER (500000 MW); SILICON DIOXIDE; GLYCERYL MONOSTEARATE; PEG-100 STEARATE; YELLOW WAX; CYCLOMETHICONE 5; CARBOMER INTERPOLYMER TYPE A (ALLYL SUCROSE CROSSLINKED); CHLORPHENESIN; BENZYL ALCOHOL; TROLAMINE; EDETATE DISODIUM ANHYDROUS; BUTYLATED HYDROXYTOLUENE

RYSHI_Daylogic 922.000/922AA
Sheer Touch Sunscreen SPF 100

Active ingredient

Avobenzone 3%
Homosalate 15%
Octisalate 5%
Octocrylene 10%

Purpose

Sunscreen

Uses

- helps prevent sunburn
- if used as directed with other sun protection measures (see Directions), decreases the risk of skin cancer and early skin aging caused by the sun

Warnings

For external use only

Do not use

on damaged or broken skin

When using this product

keep out of eyes. Rinse with water to remove.

Stop use and ask a doctor if

rash occurs

Keep out of reach of children

If swallowed, get medical help or contact a Poison Control Center right away

Directions

- apply liberally 15 minutes before sun exposure
- apply to all skin exposed to the sun
- reapply: after 80 minute of swimming or sweating
- immediately after towel drying
- at least every 2 hours
- Sun Protection Measures. Spending time in the sun increases your rist of skin cancer and early skin aging. To decrease this risk, regularly use a sunscreen with Broad Spectrum SPF value of 15 or higher and other sun protection measures including:
- limit time in the sun, especially from 10 a.m. - 2 p.m.
- wear long-sleeved shirts, pants, hats and sunglasses
- children under 6 months of age: ask a doctor

Other information

protect the product in this container from excessive heat and dirtect sun

Inactive ingredients

water, diethylhexyl 2,6-naphthalate, styrene/acrylates copolymer, silica, glyceryl stearate, PEG-100 stearate, beeswax, cyclopentasiloxane, acrylates/dimethicone copolymer, acrylates/C10-30 alkyl acrylate crosspolymer, fragrance, chlorphenesin, benzyl alcohol, triethanolamine, disodium EDTA, BHT

ADVERSE REACTION

DISTRIBUTED BY: RITE AID

30 HUNTER LAME

CAMP HIL, PA 17011

SATISFACTION GUARANTEE:

If you're not satisfied, we'll happily

refund your money.

Disclaimers

May stain or damage some fabrics or surfaces

*This product is not manufactured or distributed by Johnson & Johnson Consumer, Inc., distributor of Neutrogena Ultra Sheer Dry-Touch Sunscreen Broad Spectrum SPF 100

principal display panel

daylogic™

FREE FROM OXYBENZONE - PHTHALATES

sheer touch

SUNSCREEN LOTION

BROAD SPECTRUM SPF 100

UVA/UVB Protection

Water Resistant (80 minutes)

Oil-free

Clean & Lightweight Feel

SPF 100

COMPARE TO NEUTROGENA®ULTRA SHEER SUNSCREEN BROAD SPECTRUM SPF 100+*

3 FL OZ (88 mL)